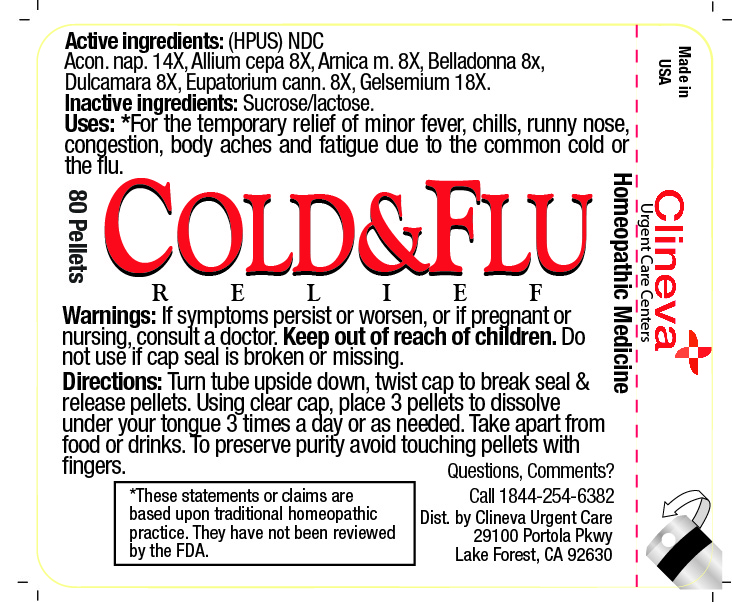 DRUG LABEL: COLD and FLU RELIEF
NDC: 71409-303 | Form: PELLET
Manufacturer: Clineva Management Services, LLC
Category: homeopathic | Type: HUMAN OTC DRUG LABEL
Date: 20260112

ACTIVE INGREDIENTS: GELSEMIUM SEMPERVIRENS ROOT 18 [hp_X]/1 1; ATROPA BELLADONNA 8 [hp_X]/1 1; EUPATORIUM CANNABINUM WHOLE 8 [hp_X]/1 1; ALLIUM CEPA WHOLE 8 [hp_X]/1 1; ACONITUM NAPELLUS 14 [hp_X]/1 1; ARNICA MONTANA 8 [hp_X]/1 1; SOLANUM DULCAMARA WHOLE 8 [hp_X]/1 1
INACTIVE INGREDIENTS: LACTOSE; SUCROSE

COLD & FLURELIEF

Inactive Ingredients

Sucrose

Lactose

Active ingredients

Acon. nap 14X, Allium cepa 8X, Arnica m. 8X, Belladonna 8X, Dulcamara 8X, Eupatorium cann. 8X, Gelsemium 18X

Directions:

Turn tube upside down, twist cap to break seal & release pellets. Using clear cap, place 3 pellets to dissilve under your tongue 3 times a day or as needed. Take apart from food or drinks. To preserve purity avoid touching pellets with fingers.

Warnings:

Keep out of reach of children.

Uses:

*For the temporary relief of minor fever, chills, runny nose, congestion, body aches adn fatigue due to the common cold or the flu.

Warnings:

If symptoms persist or worsen, or if pregnant or nursing, consult a doctor. Do not use if cap seal is broken or missing.

Question, Comments?

Call 1-844-254-6382

INDICATIONS AND USAGE

For the temporary relief of minor fever, chills, runny nose, congestion, body aches and fatigue due to the common cold or the flu

WARNINGS

If symptoms persist or worsen, or if pregnant or nursing, consult a doctor.